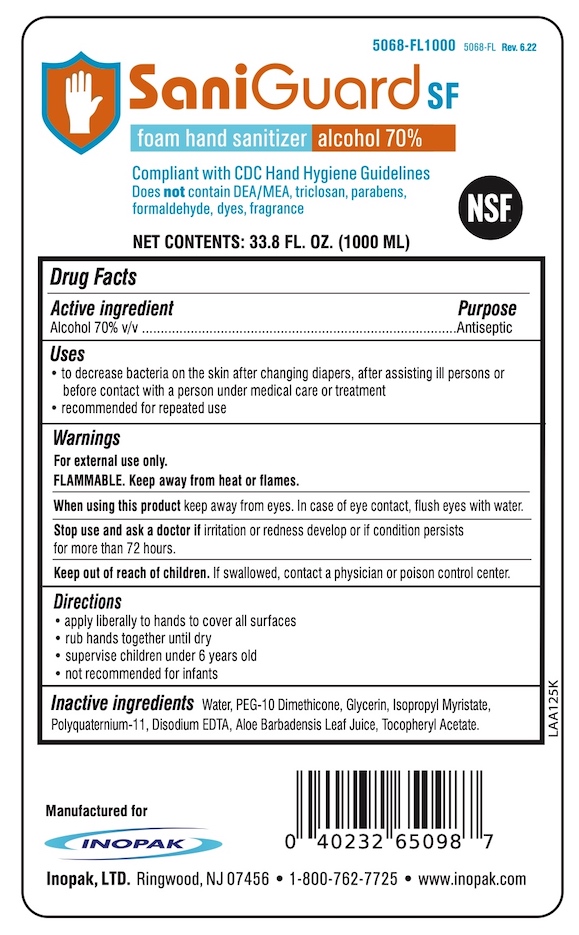 DRUG LABEL: SaniGuard-SF
NDC: 58575-150 | Form: LIQUID
Manufacturer: Inopak. Ltd
Category: otc | Type: HUMAN OTC DRUG LABEL
Date: 20220630

ACTIVE INGREDIENTS: ALCOHOL 70 mL/100 mL
INACTIVE INGREDIENTS: EDETATE DISODIUM; ALPHA-TOCOPHEROL ACETATE; ISOPROPYL MYRISTATE; PEG-10 DIMETHICONE (600 CST); ALOE VERA LEAF; POLYQUATERNIUM-11 (1000000 MW); WATER; GLYCERIN

Inopak SaniGuard-SF

Drug Facts

Active ingredient

Alcohol 70% v/v

Purpose

Antiseptic

Uses

- to decrease bacteria on the skin after changing diapers, assisting ill persons or before contact with a person under medical care or treatment
- Recommended for repeated use

Warnings

For external use only.

FLAMMABLE, keep away from heat or flames.

When using this product keep away from eyes. In case of eye contact, flush eyes with water.

Stop use and ask a doctor if irritation and redness develop or if condition persists for more than 72 hours.

Keep out of reach of children. If swallowed, contact a physician or poison control center.

Directions

- apply liberally to hands to cover all surfaces.
- rub hands together until dry.
- supervise children under 6 years old.
- not recommended for infants.

INACTIVE INGREDIENT

Inactive ingredients Water, PEG-10 Dimethicone, Glycerin, Isopropyl Myristate, Polyquaternium-11, Disodium EDTA, Aloe Barbadensis Leaf Juice, Tocopheryl Acetate

Manufacturd for

Inopak, LTD. Ringwood, NJ 07456 • 1-800-762-7725 • www.inopak.com

PACKAGE LABEL

SaniGuard SF

foam hand sanitizer

alcohol 70%

Compliant with CDC Hand Hygiene Guidlines

Does not contain DEA/MEA, triclosan, parabens, formaldehyde, dyes, fragrance

NET CONTENTS: 33.8 FL. OZ. (1000 ML)